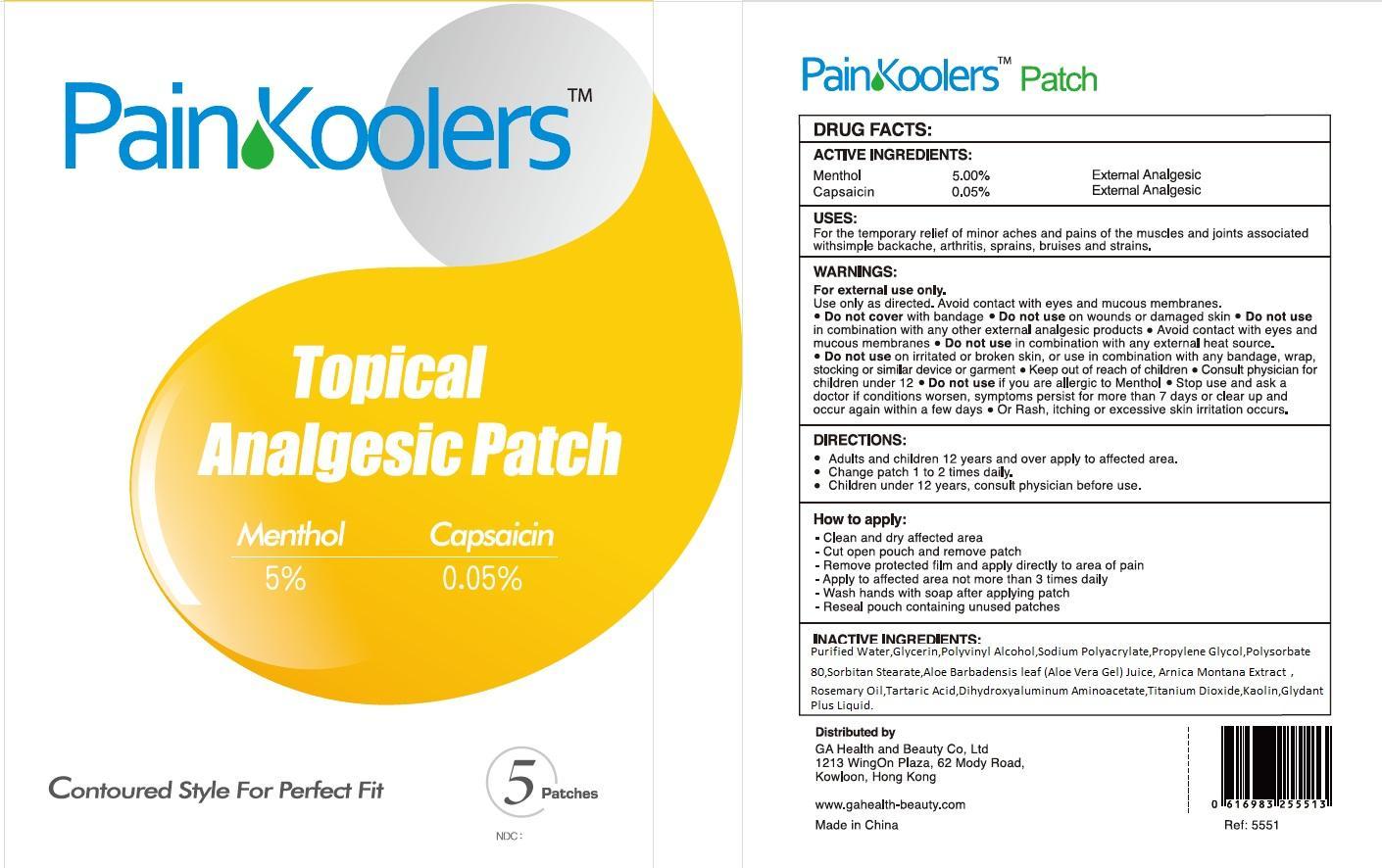 DRUG LABEL: PainKoolers Topical Analgesic
NDC: 70118-002 | Form: GEL
Manufacturer: GA Health and Beauty (FOSHAN) Co., Ltd
Category: otc | Type: HUMAN OTC DRUG LABEL
Date: 20151130

ACTIVE INGREDIENTS: MENTHOL, UNSPECIFIED FORM 5 g/100 g; CAPSAICIN 0.05 g/100 g
INACTIVE INGREDIENTS: WATER; GLYCERIN; POLYVINYL ALCOHOL; PROPYLENE GLYCOL; POLYSORBATE 80; SORBITAN MONOSTEARATE; ALOE VERA LEAF; ARNICA MONTANA; ROSEMARY OIL; TARTARIC ACID; DIHYDROXYALUMINUM AMINOACETATE; TITANIUM DIOXIDE; KAOLIN

PainKoolers Topical Analgesic Patch

ACTIVE INGREDIENTS:

Menthol 5.00%

Capsaicin 0.05%

PURPOSE

External Analgesic

USES:

For the temporary relief of minor aches and pains of the muscles and joints associated with simple backache, arthritis, sprains, bruises and strains.

WARNINGS:

For external use only.

Use only as directed. Avoid contact with eyes and muccous membranes.

• Do not cover with bandage

Do not use

on wounds or damaged skin • Do not use in combination with any other external analgesic products • Avoid contact with eyes and maccous membranes • Do not use in combination with any external heat source. • Do not use on irritated or broken skin, or use in combination with any bandage, wrap, stocking or similar device or garment

Keep out of reach of children

• Consult physician for children under 12

• Do not use

if you are allergic or amenthol

• Stop use

and ask a doctor id conditions worsen, symptoms persist for more than 7 days or clear up and occur again within a few days • Or Rash, itching or excessive skin irritation occurs.

DIRECTIONS:

- Adults and children 12 years and over apply to affected area.
- Change patch 1 to 2 times daily.
- Children under 12 years, consult physician before use.

How to apply:

- Clean and dry affected area
- Cut open pouch and remove patch
- Remove protected film and apply directly to area of pain
- Apply to affected area not more than 3 times daily
- Wash hands with soap after applying patch
- Reseal pouch containing unused patches

INACTIVE INGREDIENTS:

Purified Water,Glycerin,Polyvinyl Alcohol,Sodium Polyacrylate,Propylene Glycol,Polysorbate 80,Sorbitan Stearate,Aloe Barbadensis leaf (Aloe Vera Gel) Juice, Aanica Montana Extract, Rosemary Oil,Tartaric Acid,Dihydroxyaluminum Aminoacetate,Titanium Dioxide,Kaolin,Glydant Plus Liquid.